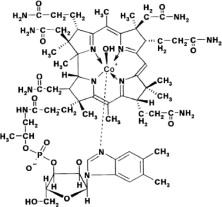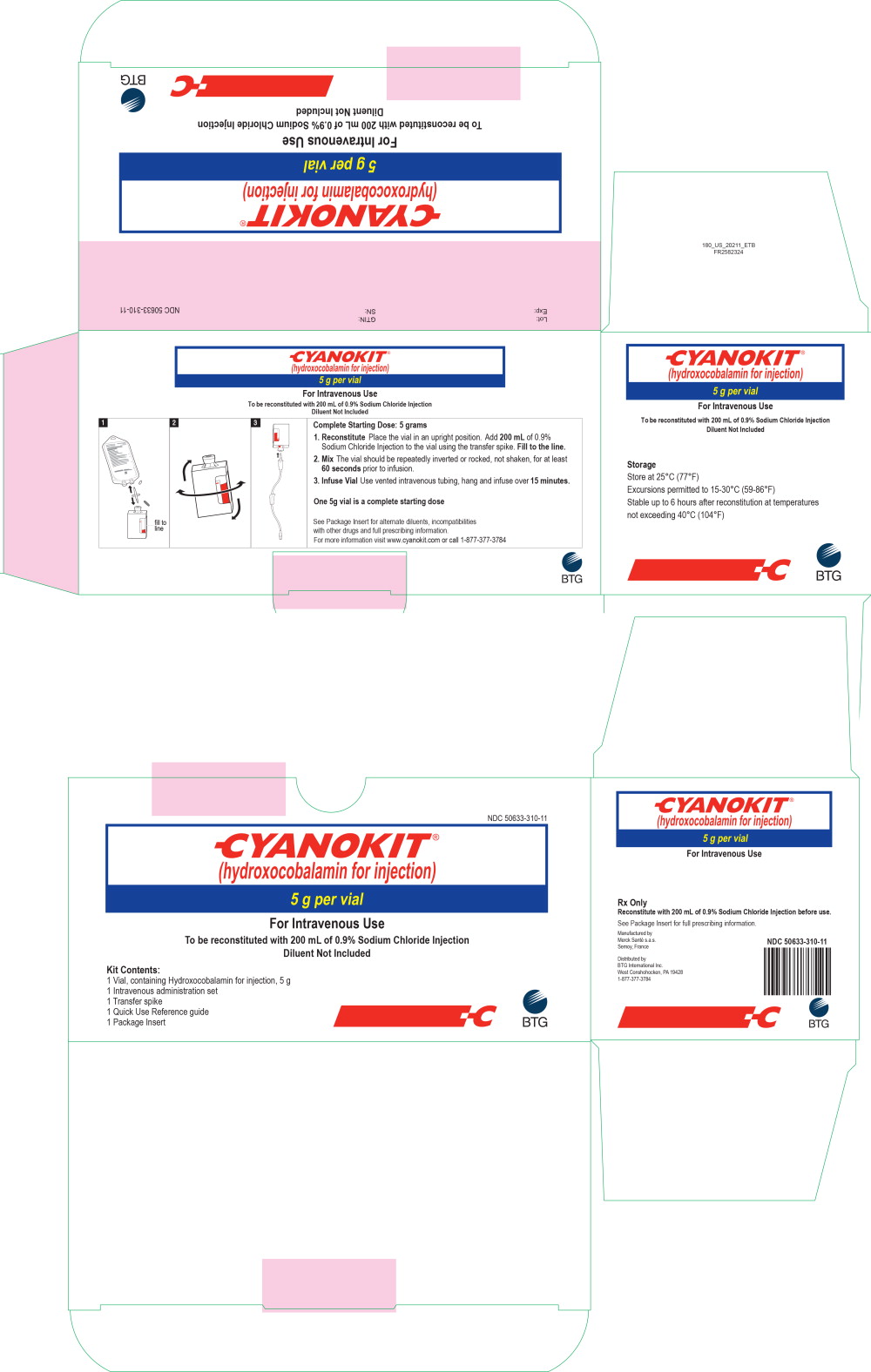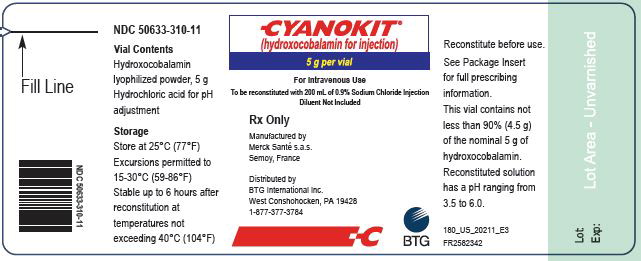 DRUG LABEL: Cyanokit
NDC: 50633-310 | Form: INJECTION, POWDER, LYOPHILIZED, FOR SOLUTION
Manufacturer: BTG INTERNATIONAL INC.
Category: prescription | Type: HUMAN PRESCRIPTION DRUG LABEL
Date: 20230427

ACTIVE INGREDIENTS: Hydroxocobalamin 5 g/250 mL
INACTIVE INGREDIENTS: hydrochloric acid

HIGHLIGHTS OF PRESCRIBING INFORMATION

These highlights do not include all the information needed to use CYANOKIT safely and effectively. See full prescribing information for CYANOKIT.
CYANOKIT® (hydroxocobalamin for injection) for intravenous infusion
Initial U.S. Approval: 1975

1 INDICATIONS AND USAGE

CYANOKIT is indicated for the treatment of known or suspected cyanide poisoning. (1)

2 DOSAGE AND ADMINISTRATION

- If clinical suspicion of cyanide poisoning is high, administer CYANOKIT without delay and in conjunction with appropriate airway, ventilatory, and circulatory support, oxygen administration as well as management of seizures. (2.1)
- The expert advice of a regional poison control center may be obtained by calling 1-800-222-1222. (2.1)

Dosing:

- The starting dose of CYANOKIT for adults is 5 g, administered by intravenous infusion over 15 minutes. One 5 g vial is a complete starting dose. (2.2)
- Depending upon the severity of the poisoning and the clinical response, a second dose of 5 g may be administered by intravenous infusion for a total dose of 10 g. (2.2)
- The rate of infusion for the second 5 g dose may range from 15 minutes (for patients in extremis) to 2 hours based on patient condition. (2.2)
- The recommended diluent is 0.9% Sodium Chloride injection. (2.3)
- CYANOKIT requires a separate intravenous line for administration. (2.4)

3 DOSAGE FORMS AND STRENGTHS

- CYANOKIT (hydroxocobalamin for injection) for intravenous infusion consists of 1 vial, containing 5 g lyophilized hydroxocobalamin dark red crystalline powder for injection. After reconstitution, the vial contains hydroxocobalamin for injection, 25 mg/mL. (3)

4 CONTRAINDICATIONS

None (4)

5 WARNINGS AND PRECAUTIONS

- Risk of Anaphylaxis and Other Hypersensitivity Reactions: Consider alternative therapies, if available, in patients with known anaphylactic reactions to hydroxocobalamin or cyanocobalamin. (5.2)
- Risk of Renal Injury: Acute renal failure with acute tubular necrosis, renal impairment and urine calcium oxalate crystals have been reported following CYANOKIT therapy. Monitor renal function for 7 days following CYANOKIT therapy. (5.3)
- Risk of Increased Blood Pressure: Substantial increases in blood pressure may occur following CYANOKIT therapy. Monitor blood pressure during treatment. (5.4)

6 ADVERSE REACTIONS

Most common adverse reactions (>5%) include transient chromaturia, erythema, oxalate crystals in urine, rash, increased blood pressure, nausea, headache, and infusion site reactions. (6.1)

To report SUSPECTED ADVERSE REACTIONS contact BTG at 1-877-377-3784, or FDA at 1-800-FDA-1088 or www.fda.gov/medwatch.

8 USE IN SPECIFIC POPULATIONS

- Pregnancy: Based on animal studies, may cause fetal harm; however, CYANOKIT administration for cyanide poisoning may be lifesaving for the pregnant woman and fetus. Treatment should not be withheld due to pregnancy (8.1)
- Lactation: Breastfeeding not recommended (8.2)

FULL PRESCRIBING INFORMATION

1 INDICATIONS AND USAGE

CYANOKIT is indicated for the treatment of known or suspected cyanide poisoning.

2 DOSAGE AND ADMINISTRATION

2.1 Important Dosage and Administration Instructions

- If clinical suspicion of cyanide poisoning is high, administer CYANOKIT without delay.
- Comprehensive treatment of acute cyanide intoxication requires support of vital functions. Airway, ventilatory and circulatory support, oxygen administration, and management of seizures should not be delayed to administer CYANOKIT [see Warnings and Precautions (5.1)].
- The expert advice of a regional poison control center may be obtained by calling 1-800-222-1222.

Identifying Patients with Cyanide Poisoning

Cyanide poisoning may result from inhalation, ingestion, or dermal exposure to various cyanide-containing compounds, including smoke from closed-space fires. Sources of cyanide poisoning include hydrogen cyanide and its salts, cyanogenic plants, aliphatic nitriles, and prolonged exposure to sodium nitroprusside.

The presence and extent of cyanide poisoning are often initially unknown. There is no widely available, rapid, confirmatory cyanide blood test. Treatment decisions must be made on the basis of clinical history and signs and symptoms of cyanide intoxication.

Table 1 Common Signs and Symptoms of Cyanide Poisoning
Symptoms; - Headache - Confusion - Dyspnea - Chest tightness - Nausea | Signs; - Altered Mental Status (e.g., confusion, disorientation) - Seizures or Coma - Mydriasis - Tachypnea / Hyperpnea (early) - Bradypnea / Apnea (late) - Hypertension (early) / Hypotension (late) - Cardiovascular collapse - Vomiting - Plasma lactate concentration ≥8 mmol/L

In some settings, panic symptoms including tachypnea and vomiting may mimic early cyanide poisoning signs. The presence of altered mental status (e.g., confusion and disorientation) and/or mydriasis is suggestive of true cyanide poisoning although these signs can occur with other toxic exposures as well.

Smoke Inhalation

Not all smoke inhalation victims will have cyanide poisoning and may present with burns, trauma, and exposure to other toxic substances making a diagnosis of cyanide poisoning particularly difficult. Prior to administration of CYANOKIT, smoke-inhalation victims should be assessed for the following:

- Exposure to fire or smoke in an enclosed area
- Presence of soot around the mouth, nose or oropharynx
- Altered mental status

Although hypotension is highly suggestive of cyanide poisoning, it is only present in a small percentage of cyanide-poisoned smoke inhalation victims. Also indicative of cyanide poisoning is a plasma lactate concentration ≥10 mmol/L (a value higher than that typically listed in the table of signs and symptoms of isolated cyanide poisoning because carbon monoxide associated with smoke inhalation also contributes to lactic acidemia). If cyanide poisoning is suspected, treatment should not be delayed to obtain a plasma lactate concentration.

Use with Other Cyanide Antidotes

The safety of administering other cyanide antidotes simultaneously with CYANOKIT has not been established. If a decision is made to administer another cyanide antidote with CYANOKIT, these drugs should not be administered concurrently in the same intravenous line [see Dosage and Administration (2.4)].

2.2 Recommended Dosing

The starting dose of hydroxocobalamin for adults is 5 g administered as an intravenous infusion over 15 minutes (approximately 15 mL/min). Administration of the entire vial constitutes a complete starting dose. Depending upon the severity of the poisoning and the clinical response, a second dose of 5 g may be administered by intravenous infusion for a total dose of 10 g. The rate of infusion for the second dose may range from 15 minutes (for patients in extremis) to two hours, as clinically indicated.

2.3 Preparation of Solution for Infusion

Reconstitute the 5 g vial of hydroxocobalamin with 200 mL of diluent (not provided with CYANOKIT) using the supplied sterile transfer spike. The recommended diluent is 0.9% Sodium Chloride injection (0.9% NaCl). Lactated Ringers injection and 5% Dextrose injection (D5W) have also been found to be compatible with hydroxocobalamin and may be used if 0.9% NaCl is not readily available. The line on the vial label represents 200 mL volume of diluent. Following the addition of diluent to the lyophilized powder, the vial should be repeatedly inverted or rocked, not shaken, for at least 60 seconds prior to infusion.

Visually inspect hydroxocobalamin solutions for particulate matter and color prior to administration. If the reconstituted solution is not dark red or if particulate matter is observed after the solution has been appropriately mixed, the solution should be discarded.

2.4 Incompatibility Information

Physical incompatibility (particle formation) and chemical incompatibility were observed with the mixture of hydroxocobalamin in solution with selected drugs that are frequently used in resuscitation efforts. Hydroxocobalamin is also chemically incompatible with sodium thiosulfate and sodium nitrite and has been reported to be incompatible with ascorbic acid. Therefore, these and other drugs should not be administered simultaneously through the same intravenous line as hydroxocobalamin.

Simultaneous administration of hydroxocobalamin and blood products (whole blood, packed red cells, platelet concentrate and/or fresh frozen plasma) through the same intravenous line is not recommended. However, blood products and hydroxocobalamin can be administered simultaneously using separate intravenous lines (preferably on contralateral extremities, if peripheral lines are being used).

2.5 Storage of Reconstituted Drug Product

Once reconstituted, hydroxocobalamin is stable for up to 6 hours at temperatures not exceeding 40°C (104°F). Do not freeze. Any reconstituted product not used by 6 hours should be discarded.

3 DOSAGE FORMS AND STRENGTHS

CYANOKIT (hydroxocobalamin for injection) for intravenous infusion consists of 1 vial, containing 5 g lyophilized hydroxocobalamin dark red crystalline powder for injection. After reconstitution, the vial contains hydroxocobalamin for injection, 25 mg/mL [see How Supplied/Storage and Handling (16) for full kit description].

4 CONTRAINDICATIONS

None

5 WARNINGS AND PRECAUTIONS

5.1 Emergency Patient Management

In conjunction with CYANOKIT, treatment of cyanide poisoning must include immediate attention to airway patency, adequacy of oxygenation and hydration, cardiovascular support, and management of seizures. Consideration should be given to decontamination measures based on the route of exposure.

5.2 Risk of Anaphylactic and Other Hypersensitivity Reactions

Use caution in the management of patients with known anaphylactic reactions to hydroxocobalamin or cyanocobalamin. Consider alternative therapies, if available.

Allergic reactions may include: anaphylaxis, chest tightness, edema, urticaria, pruritus, dyspnea, and rash.

Allergic reactions including angioneurotic edema have also been reported in postmarketing experience.

5.3 Risk of Renal Injury

Cases of acute renal failure with acute tubular necrosis, renal impairment, and urine calcium oxalate crystals have been reported. In some situations, hemodialysis was required to achieve recovery. Regular monitoring of renal function, including but not limited to blood urea nitrogen (BUN) and serum creatinine, should be performed for 7 days following CYANOKIT therapy.

5.4 Risk of Increased Blood Pressure

Many patients with cyanide poisoning will be hypotensive; however, elevations in blood pressure have also been observed in known or suspected cyanide poisoning victims.

Elevations in blood pressure (≥180 mmHg systolic or ≥110 mmHg diastolic) were observed in approximately 18% of healthy subjects (not exposed to cyanide) receiving hydroxocobalamin 5 g and 28% of subjects receiving 10 g. Increases in blood pressure were noted shortly after the infusions were started; the maximal increase in blood pressure was observed toward the end of the infusion. These elevations were generally transient and returned to baseline levels within 4 hours of dosing. Monitor blood pressure during treatment with CYANOKIT.

5.5 Interference with Clinical Laboratory Evaluations and Clinical Methods

Clinical Laboratory Evaluations

Because of its deep red color, hydroxocobalamin has been found to interfere with colorimetric determination of certain laboratory parameters (e.g., clinical chemistry, hematology, coagulation, and urine parameters). In vitro tests indicated that the extent and duration of the interference are dependent on numerous factors such as the dose of hydroxocobalamin, analyte, methodology, analyzer, hydroxocobalamin concentration, and partially on the time between sampling and measurement.

The data presented in Table 2 is collected from in vitro studies and pharmacokinetic data in healthy volunteers and describes laboratory interference that may be observed following a 5 g dose of hydroxocobalamin. Interference following a 10 g dose can be expected to last up to an additional 24 hours. The extent and duration of interference in cyanide-poisoned patients may differ. In addition, results may vary substantially from one analyzer to another. Be aware of this when reporting and interpreting laboratory results.

Table 2 Laboratory Interference Observed with in vitro Samples of Hydroxocobalamin
Laboratory Parameter | No Interference Observed | Artificially Increased * | Artificially Decreased * | Un-predictable | Duration of Interference
Clinical Chemistry | Calcium Sodium Potassium Chloride Urea GGT | Creatinine Bilirubin Triglycerides Cholesterol Total protein Glucose Albumin Alkaline phosphatase | ALT Amylase | Phosphate Uric Acid AST CK CKMB LDH | 24 hours with the exception of bilirubin (up to 4 days)
Hematology | Erythrocytes Hematocrit MCV Leukocytes Lymphocytes Monocytes Eosinophils Neutrophils Platelets | Hemoglobin MCH MCHC Basophils |  |  | 12 - 16 hours
Coagulation |  |  |  | aPTT PT (Quick or INR) | 24 - 48 hours
Urinalysis |  | pH (with all doses) Glucose Protein Erythrocytes Leukocytes Ketones Bilirubin Urobilinogen Nitrite | pH (with equivalent doses of <5 g) |  | 48 hours up to 8 days; color changes may persist up to 28 days
* ≥10% interference observed on at least 1 analyzer
Analyzers used: ACL Futura (Instrumentation Laboratory), AxSYM®/Architect™ (Abbott), BM Coasys^110 (Boehringer Mannheim), CellDyn 3700® (Abbott), Clinitek® 500 (Bayer), Cobas Integra® 700, 400 (Roche), Gen-S Coultronics, Hitachi 917, STA® Compact, Vitros® 950 (Ortho Diagnostics)

Clinical Methods

Because of its deep red color, hydroxocobalamin may cause hemodialysis machines to shut down due to an erroneous detection of a “blood leak”. This should be considered before hemodialysis is initiated in patients treated with hydroxocobalamin.

5.6 Photosensitivity

Hydroxocobalamin absorbs visible light in the UV spectrum. It therefore has potential to cause photosensitivity. While it is not known if the skin redness predisposes to photosensitivity, patients should be advised to avoid direct sun while their skin remains discolored.

5.7 Use of Blood Cyanide Assay

While determination of blood cyanide concentration is not required for management of cyanide poisoning and should not delay treatment with CYANOKIT, collecting a pretreatment blood sample may be useful for documenting cyanide poisoning as sampling post-CYANOKIT use may be inaccurate.

6 ADVERSE REACTIONS

Serious adverse reactions with hydroxocobalamin include allergic reactions, renal injury, and increases in blood pressure [see Warnings and Precautions (5.2, 5.3, 5.4)].

6.1 Clinical Studies Experience

Experience in Healthy Subjects

Because clinical trials were conducted under widely varying conditions, adverse reaction rates observed in the clinical trials may not reflect the rates observed in practice.

A double-blind, randomized, placebo-controlled, single-ascending-dose (2.5, 5, 7.5, and 10 g) study was conducted to assess the safety, tolerability, and pharmacokinetics of hydroxocobalamin in 136 healthy adult subjects. Because of the dark red color of hydroxocobalamin, the two most frequently occurring adverse reactions were chromaturia (red-colored urine) which was reported in all subjects receiving a 5 g dose or greater; and erythema (skin redness), which occurred in most subjects receiving a 5 g dose or greater. Adverse reactions reported in at least 5% of the 5 g dose group and corresponding rates in the 10 g and placebo groups are shown in Table 3.

Table 3 Incidence of Adverse Reactions Occurring in >5% of Subjects in 5 g Dose Group and Corresponding Incidence in 10 g Dose Group and Placebo
ADR | 5 g Dose Group |  | 10 g Dose Group
ADR | Hydroxocobalamin N=66 n (%) | Placebo N=22 n (%) | Hydroxocobalamin N=18 n (%) | Placebo N=6 n (%)
Chromaturia (red colored urine) | 66 (100) | 0 | 18 (100) | 0
Erythema | 62 (94) | 0 | 18 (100) | 0
Oxalate crystals in urine | 40 (61) | 1 (5) | 10 (56) | 0
Rash* | 13 (20) | 0 | 8 (44) | 0
Blood pressure increased | 12 (18) | 0 | 5 (28) | 0
Nausea | 4 (6) | 1 (5) | 2 (11) | 0
Headache | 4 (6) | 1 (5) | 6 (33) | 0
Lymphocyte percent decreased | 5 (8) | 0 | 3 (17) | 0
Infusion site reaction | 4 (6) | 0 | 7 (39) | 0
* Rashes were predominantly acneiform

In this study, the following adverse reactions were reported to have occurred in a dose-dependent fashion and with greater frequency than observed in placebo-treated cohorts: increased blood pressure (particularly diastolic blood pressure), rash, nausea, headache and infusion site reactions. All were mild to moderate in severity and resolved spontaneously when the infusion was terminated or with standard supportive therapies.

Other adverse reactions reported in this study and considered clinically relevant were:

- Eye disorders: swelling, irritation, redness
- Gastrointestinal disorders: dysphagia, abdominal discomfort, vomiting, diarrhea, dyspepsia, hematochezia
- General disorders and administration site conditions: peripheral edema, chest discomfort
- Immune system disorders: allergic reaction
- Nervous system disorders: memory impairment, dizziness
- Psychiatric disorders: restlessness
- Respiratory, thoracic and mediastinal disorders: dyspnea, throat tightness, dry throat
- Skin and subcutaneous tissue disorders: urticaria, pruritus
- Vascular disorders: hot flush

Experience in Known or Suspected Cyanide Poisoning Victims

Four open-label, uncontrolled, clinical studies (one of which was prospective and three of which were retrospective) were conducted in known or suspected cyanide-poisoning victims. A total of 245 patients received hydroxocobalamin treatment in these studies. Systematic collection of adverse events was not done in all of these studies and interpretation of causality is limited due to the lack of a control group and due to circumstances of administration (e.g., use in fire victims). Adverse reactions reported in these studies listed by system organ class included:

- Cardiac disorders: ventricular extrasystoles
- Investigations: electrocardiogram repolarization abnormality, heart rate increased
- Respiratory, thoracic, and mediastinal disorders: pleural effusion

Adverse reactions common to both the studies in known or suspected cyanide poisoning victims and the study in healthy volunteers are listed in the healthy volunteer section only and are not duplicated in this list.

6.2 Postmarketing Experience

The following adverse reactions have been identified during postapproval use of CYANOKIT. Because adverse reactions are reported voluntarily from a population of uncertain size, it is not always possible to reliably estimate their frequency.

Cases of acute renal failure with acute tubular necrosis, renal impairment, and urine calcium oxalate crystals have been reported in patients treated with CYANOKIT.

7 DRUG INTERACTIONS

Formal drug interaction studies have not been conducted with CYANOKIT.

Interference with Laboratory Tests

Because of its deep red color, hydroxocobalamin has been found to interfere with colorimetric determination of certain laboratory parameters (e.g., clinical chemistry, hematology, coagulation, and urine parameters). Be aware of this when reporting and interpreting laboratory results [see Warnings and Precautions (5.5)].

8 USE IN SPECIFIC POPULATIONS

8.1 Pregnancy

Risk Summary

Available data from cases reported in the published literature and postmarketing surveillance with CYANOKIT use in pregnant women are insufficient to identify a drug-associated risk for major birth defects, miscarriage, or adverse maternal and fetal outcomes. There are risks to the pregnant woman and fetus associated with untreated cyanide poisoning (see Clinical Considerations). In animal studies, hydroxocobalamin administered to pregnant rats and rabbits during the period of organogenesis caused skeletal and soft tissue abnormalities, including alterations in the central nervous system, at exposures similar to human exposures at the therapeutic dose (see Data).

The estimated background risk of major birth defects and miscarriage for the indicated population is unknown. All pregnancies have a background risk of birth defect, loss, or other adverse outcomes. In the U.S. general population, the estimated background risk of major birth defects and miscarriage in clinically recognized pregnancies is 2-4% and 15-20%, respectively.

Clinical Considerations

Disease-associated maternal and/or embryo/fetal risk

Cyanide readily crosses the placenta. Cyanide poisoning is a medical emergency in pregnancy which can be fatal for the pregnant woman and fetus if left untreated. Life-sustaining therapy should not be withheld due to pregnancy.

Data

Animal Data

In animal studies, pregnant rats and rabbits received CYANOKIT (75, 150, or 300 mg/kg/d) during the period of organogenesis. Following intraperitoneal dosing in rats and intravenous dosing in rabbits, maternal exposures were equivalent to 0.5, 1, or 2 times the human exposure at the therapeutic dose (based on AUC). In the high dose groups for both species, maternal toxicity occurred, and there was a reduced number of live fetuses due to embryofetal resorptions. In addition, decreased live fetal weight occurred in high dose rats, but not in rabbits. Incomplete skeletal ossification occurred in both rats and rabbits. In rats, two fetuses of the high dose group and two fetuses of the mid dose group (each from a different litter) had short, rudimentary or small front or hind legs. Rabbit litters and fetuses exhibited a dose-dependent increase in various gross soft tissue and skeletal anomalies. The main findings in rabbits were flexed, rigid flexor or medially rotated forelimbs or hindlimbs and domed heads at external examination; enlarged anterior or posterior fontanelles of the ventricles of the brain and flat, bowed or large ribs at skeletal examination; and dilated ventricles of the brain, and thick wall of the stomach at visceral examination. It is unknown if similar findings would be observed in rats and rabbits if CYANOKIT was administered as a single dose during any critical period of development.

8.2 Lactation

Risk Summary

Breastfeeding is not recommended during treatment with CYANOKIT. There are no data to determine when breastfeeding may be safely restarted following administration of CYANOKIT. Hydroxocobalamin and Vitamin B12 (which is formed when hydroxocobalamin combines with cyanide) are present in human milk. There are no data on the effects of hydroxocobalamin on the breastfed infant or the effects on milk production.

8.4 Pediatric Use

Safety and effectiveness of CYANOKIT have not been established in this population. In non-US marketing experience, a dose of 70 mg/kg has been used to treat pediatric patients.

8.5 Geriatric Use

Approximately 50 known or suspected cyanide poisoning victims aged 65 or older received hydroxocobalamin in clinical studies. In general, the safety and effectiveness of hydroxocobalamin in these patients was similar to that of younger patients. No adjustment of dose is required in elderly patients.

8.6 Renal Impairment

The safety and effectiveness of CYANOKIT have not been studied in patients with renal impairment. Hydroxocobalamin and cyanocobalamin are eliminated unchanged by the kidneys.

8.7 Hepatic Impairment

The safety and effectiveness of CYANOKIT have not been studied in patients with hepatic impairment.

10 OVERDOSAGE

No data are available about overdose with CYANOKIT in adults. Should overdose occur, treatment should be directed to the management of symptoms. Hemodialysis may be effective in such a circumstance, but is only indicated in the event of significant hydroxocobalamin-related toxicity. Because of its deep red color, hydroxocobalamin may interfere with the performance of hemodialysis machines [see Warnings and Precautions (5.5)].

11 DESCRIPTION

Hydroxocobalamin, the active ingredient in CYANOKIT, is cobinamide dihydroxide dihydrogen phosphate (ester), mono (inner salt), 3'-ester with 5,6-dimethyl-1-α-D-ribofuranosyl-1H-benzimidazole, an antidote. The drug substance is the hydroxylated active form of vitamin B12 and is a large molecule in which a trivalent cobalt ion is coordinated in four positions by a tetrapyrol (or corrin) ring. It is a hygroscopic, odorless, dark red, crystalline powder that is freely soluble in water and ethanol, and practically insoluble in acetone and diethyl ether. Hydroxocobalamin has a molecular weight of 1346.36 atomic mass units, an empirical formula of C62H89CoN13O15P and the following structural formula:

CYANOKIT (hydroxocobalamin for injection) for intravenous infusion is a cyanide antidote package which contains one colorless 250 mL glass vial, containing 5 g dark red lyophilized hydroxocobalamin, pH adjusted with hydrochloric acid, one transfer spike, one intravenous administration set, one quick use reference guide and one package insert.

The 5 g vial of hydroxocobalamin for injection is to be reconstituted with 200 mL of 0.9% NaCl, to give a dark red injectable solution (25 mg/mL). If 0.9% NaCl is not readily available, 200 mL of either Lactated Ringers injection or 5% Dextrose injection (D5W) may be used as the diluent. Diluent is not included in the CYANOKIT. The pH of the reconstituted product ranges from 3.5 to 6.0.

12 CLINICAL PHARMACOLOGY

12.1 Mechanism of Action

Cyanide is an extremely toxic poison. In the absence of rapid and adequate treatment, exposure to a high dose of cyanide can result in death within minutes due to the inhibition of cytochrome oxidase resulting in arrest of cellular respiration. Specifically, cyanide binds rapidly with cytochrome a3, a component of the cytochrome c oxidase complex in mitochondria. Inhibition of cytochrome a3 prevents the cell from using oxygen and forces anaerobic metabolism, resulting in lactate production, cellular hypoxia and metabolic acidosis. In massive acute cyanide poisoning, the mechanism of toxicity may involve other enzyme systems as well. Signs and symptoms of acute systemic cyanide poisoning may develop rapidly within minutes, depending on the route and extent of cyanide exposure.

The action of CYANOKIT in the treatment of cyanide poisoning is based on its ability to bind cyanide ions. Each hydroxocobalamin molecule can bind one cyanide ion by substituting it for the hydroxo ligand linked to the trivalent cobalt ion, to form cyanocobalamin, which is then excreted in the urine.

12.2 Pharmacodynamics

Administration of CYANOKIT to cyanide-poisoned patients with the attendant formation of cyanocobalamin resulted in increases in blood pressure and variable changes in heart rate upon initiation of hydroxocobalamin infusions [see Warnings and Precautions (5.4)].

12.3 Pharmacokinetics

Following intravenous administration of hydroxocobalamin significant binding to plasma proteins and low molecular weight physiological compounds occurs, forming various cobalamin-(III) complexes by replacing the hydroxo ligand. The low molecular weight cobalamins-(III) formed, including hydroxocobalamin, are termed “free cobalamins-(III)”; the sum of free and protein-bound cobalamins is termed “total cobalamins-(III)”. In order to reflect the exposure to the sum of all derivatives, pharmacokinetics of cobalamins-(III) (i.e., cobalamin-(III) entity without specific ligand) were investigated instead of hydroxocobalamin alone, using the concentration unit μg eq/mL.

Dose-proportional pharmacokinetics was observed following single dose intravenous administration of 2.5 to 10 g of hydroxocobalamin in healthy volunteers. Mean free and total cobalamins-(III) Cmax values of 113 and 579 μg eq/mL, respectively, were determined following a dose of 5 g of hydroxocobalamin. Similarly, mean free and total cobalamins-(III) Cmax values of 197 and 995 μg eq/mL, respectively, were determined following the dose of 10 g of hydroxocobalamin.

When normalized for body weight, male and female subjects revealed no major differences in pharmacokinetic parameters of free and total cobalamins-(III) following the administration of 5 and 10 g of hydroxocobalamin.

Distribution

The volume of distribution at steady state (Vss) for both free and total cobalamins-(III) showed no apparent relationship to dose. The Vss ranged from 280.7 to 349.5 L for free cobalamins-(III), and from 21.8 to 25.6 L for total cobalamins-(III). The comparatively high values for Vss of free cobalamins-(III) are due to the high protein binding of hydroxocobalamin as it reacts in the blood with plasma constituents to form cobalamins-(III) complexes and the rapid distribution of free cobalamins-(III) into tissues.

Elimination

The mean total amount of cobalamins-(III) excreted in urine during the collection period of 72 hours was about 60% of a 5 g dose and about 50% of a 10 g dose of hydroxocobalamin. Overall, the total urinary excretion was calculated to be at least 60 to 70% of the administered dose. The majority of the urinary excretion occurred during the first 24 hours, but red-colored urine was observed for up to 35 days following the intravenous infusion. The mean half-life of free and total cobalamins-(III) was found to be approximately 26 to 31 hours at both the 5 g and 10 g dose level.

Metabolism

Hydroxocobalamin does not undergo metabolism.

Excretion

Hydroxocobalamin is mainly excreted in urine.

In cyanide poisoning victims, hydroxocobalamin binds to cyanide to form cyanocobalamin, which is mainly excreted in urine.

13 NONCLINICAL TOXICOLOGY

13.1 Carcinogenesis, Mutagenesis, Impairment of Fertility

Carcinogenesis

Long-term animal studies have not been performed to evaluate the carcinogenic potential of hydroxocobalamin.

Mutagenesis

Hydroxocobalamin was negative in the following mutagenicity assays: in vitro bacterial reverse mutation assay using Salmonella typhimurium and Escherichia coli strains, an in vitro assay of the tk locus in mouse lymphoma cells, and an in vivo rat micronucleus assay.

Impairment of Fertility

The effect of hydroxocobalamin on fertility has not been evaluated.

14 CLINICAL STUDIES

14.1 Animal Efficacy (Dog) Study of CYANOKIT for Cyanide Poisoning

The effectiveness of CYANOKIT for treatment of cyanide poisoning has not been determined in humans because inducing cyanide poisoning in humans to study the drug's efficacy is not ethical. Therefore, the effectiveness of CYANOKIT for cyanide poisoning was established based on the results of the adequate and well-controlled animal efficacy study described below. While the results of this animal study cannot be extrapolated to humans with certainty, the extrapolation is supported by the understanding of the pathophysiologic mechanisms of the toxicity of cyanide and the mechanisms of the protective effect of hydroxocobalamin as examined in dogs. In addition, the results of uncontrolled human studies and the animal study establish that hydroxocobalamin is likely to produce clinical benefit in humans.

The effectiveness of hydroxocobalamin was examined in a randomized, placebo-controlled, blinded study in cyanide-poisoned adult dogs assigned to treatment with vehicle (0.9% saline), or 75 or 150 mg/kg hydroxocobalamin. Anesthetized dogs were poisoned by intravenous administration of a lethal dose of potassium cyanide. Dogs then received vehicle or 75 or 150 mg/kg hydroxocobalamin, administered intravenously over 7.5 minutes. The 75 and 150 mg/kg doses are approximately equivalent to 5 and 10 g of hydroxocobalamin (respectively) in humans based on both body weight and the Cmax of hydroxocobalamin (total cobalamins-(III)). Survival at 4 hours and at 14 days was significantly greater in low-and high-dose groups compared with dogs receiving vehicle alone (Table 4). Hydroxocobalamin reduced whole blood cyanide concentrations by approximately 50% by the end of the infusion compared with vehicle.

Table 4 Survival of Cyanide-Poisoned Dogs
Parameter | Treatment
Parameter | Vehicle N=17 | CYANOKIT
Parameter | Vehicle N=17 | 75 mg/kg N=19 | 150 mg/kg N=18
Survival at Hour 4, n (%) | 7 (41) | 18 (95) | 18 (100)
Survival at Day 14, n (%) | 3 (18) | 15 (79) | 18 (100)

Histopathology revealed brain lesions that were consistent with cyanide-induced hypoxia. The incidence of brain lesions was markedly lower in hydroxocobalamin treated animals compared to vehicle treated groups.

14.2 Smoke Inhalation Victims

A prospective, uncontrolled, open-label study was carried out in 69 subjects who had been exposed to smoke inhalation from fires. Subjects had to be over 15 years of age, present with soot in the mouth and expectoration (to indicate significant smoke exposure), and have altered neurological status. The median hydroxocobalamin dose was 5 g with a range from 4 to 15 g.

Fifty of 69 subjects (73%) survived following treatment with hydroxocobalamin. Nineteen subjects treated with hydroxocobalamin did not survive. Fifteen patients treated with hydroxocobalamin were in cardiac arrest initially at the scene; 13 of these subjects died and 2 survived.

Of the 42 subjects with pretreatment cyanide levels considered to be potentially toxic, 28 (67%) survived. Of the 19 subjects whose pretreatment cyanide levels were considered potentially lethal, 11 (58%) survived. Of the 50 subjects who survived, 9 subjects (18%) had neurological sequelae at hospital discharge. These included dementia, confusion, psychomotor retardation, anterograde amnesia, intellectual deterioration moderate cerebellar syndrome, aphasia, and memory impairment.

Two additional retrospective, uncontrolled studies were carried out in subjects who had been exposed to cyanide from fire or smoke inhalation. Subjects were treated with up to 15 g of hydroxocobalamin. Survival in these two studies was 34 of 61 (56%) for one study, and 30 of 72 (42%) for the second.

14.3 Cyanide Poisoning by Ingestion or Inhalation

A retrospective, uncontrolled study was carried out in 14 subjects who had been exposed to cyanide from sources other than from fire or smoke (i.e., ingestion or inhalation). Subjects were treated with 5 to 20 g of hydroxocobalamin. Eleven of 12 subjects whose blood cyanide concentration was known had initial blood cyanide levels considered to be above the lethal threshold.

Ten of 14 subjects (71%) survived, following administration of hydroxocobalamin. One of the four subjects who died had presented in cardiac arrest. Of the 10 subjects who survived, only 1 subject had neurological sequelae at hospital discharge. This subject had post-anoxic encephalopathy, with memory impairment, considered to be due to cyanide poisoning.

14.4 Cross-Study Findings

Experience with Dosing Greater than 10 g of Hydroxocobalamin

Across all four uncontrolled studies, 10 patients who did not demonstrate a full response to 5 or 10 g-doses of hydroxocobalamin were treated with more than 10 g of hydroxocobalamin. One of these 10 patients survived with unspecified neurological sequelae.

Effects on Blood Pressure

Initiation of hydroxocobalamin infusion as part of the therapeutic interventions generally resulted in increases in blood pressure and variable changes in heart rate (often normalization).

Survival of Patients Presenting in Cardiac Arrest

Of the 245 patients across all four studies, 68 (28%) presented in cardiac arrest. While blood pressure and heart rate may have been restored in many of these 68 patients, only five (7%) survived.

16 HOW SUPPLIED/STORAGE AND HANDLING

Each CYANOKIT carton (NDC 50633-310-11) consists of the following:

- One 250 mL glass vial, containing lyophilized hydroxocobalamin for injection, 5 g
- One sterile transfer spike
- One sterile intravenous infusion set
- One quick use reference guide
- One package insert

Diluent is not included.

Storage

Lyophilized form

Store at 25°C (77°F); excursions permitted to 15-30°C (59 to 86°F) [see USP Controlled Room Temperature].

CYANOKIT may be exposed during short periods to the temperature variations of usual transport (15 days submitted to temperatures ranging from 5 to 40°C (41 to 104°F), transport in the desert (4 days submitted to temperatures ranging from 5 to 60°C (41 to 140°F)) and freezing/defrosting cycles (15 days submitted to temperatures ranging from -20 to 40°C (-4 to 104°F)).

Reconstituted solution

Store up to 6 hours at a temperature not exceeding 40ºC (104°F). Do not freeze. Discard any unused portion after 6 hours.

17 PATIENT COUNSELING INFORMATION

CYANOKIT is indicated for cyanide poisoning and in this setting, patients will likely be unresponsive or may have difficulty in comprehending counseling information.

Erythema and Chromaturia

Advise patients that skin redness may last up to 2 weeks and urine coloration may last for up to 5 weeks after administration of CYANOKIT. While it is not known if the skin redness predisposes to photosensitivity, patients should be advised to avoid direct sun while their skin remains discolored.

Rash

Inform patients that an acneiform rash may appear anywhere from 7 to 28 days following hydroxocobalamin treatment. This rash will usually resolve without treatment within a few weeks.

Renal Function Monitoring

Advise patients that renal function will be monitored for 7 days following treatment with CYANOKIT or, in the event of renal impairment, until renal function returns to normal.

Pregnancy

Advise pregnant women that maternal cyanide poisoning results in fetal cyanide poisoning. Treatment for cyanide poisoning may be lifesaving for both the pregnant woman and fetus. Advise females of reproductive potential to notify their provider if they were pregnant during therapy with CYANOKIT [see USE IN SPECIFIC POPULATIONS (8.1)].

Lactation

Advise women that breastfeeding is not recommended during treatment with CYANOKIT [see USE IN SPECIFIC POPULATIONS (8.2)].

Patient Information
CYANOKIT (hydroxocobalamin for injection)
for intravenous infusion

What is CYANOKIT?
CYANOKIT is prescription medicine used for the treatment of known or suspected cyanide poisoning. Cyanide is a chemical poison. Cyanide poisoning can happen from:
breathing smoke from household and industrial fires
breathing or swallowing cyanide
having your skin exposed to cyanide
The effectiveness of CYANOKIT was based on a study in animals, because intentionally exposing humans to cyanide is not ethical. The safety of CYANOKIT was studied in animals and healthy people and derived from experience in patients exposed to cyanide.
It is not known if CYANOKIT is safe and effective in children.
Cyanide poisoning is a life-threatening condition because cyanide stops your body from being able to use oxygen. You can die if your body does not have enough oxygen.

Tell your healthcare provider if you:

- have had an allergic reaction to hydroxocobalamin or cyanocobalamin
- are pregnant or think you may have been pregnant during treatment with CYANOKIT. CYANOKIT may harm your unborn baby. However, treatment for cyanide poisoning may save your life and the life of your unborn baby.
- are breastfeeding. Breastfeeding is not recommended during treatment with CYANOKIT. Talk to your healthcare provider about the best way to feed your baby during this time.Tell your healthcare provider about all of the medicines you take, including prescription and over-the-counter medicines, vitamins, and herbal supplements.

How is CYANOKIT given?

- Your healthcare provider will give you CYANOKIT through a vein by intravenous (IV) infusion over 15 minutes.
- A second dose of CYANOKIT may be given to you if needed.

What should I avoid after I receive CYANOKIT?

- CYANOKIT may cause red colored skin. Skin redness is common during treatment with CYANOKIT and may last up to 2 weeks after treatment with CYANOKIT. You should avoid sunlight while your skin is red.

What are the possible side effects of CYANOKIT?
CYANOKIT may cause serious side effects, including:

- Allergic reactions. Signs and symptoms of a serious allergic reaction include chest tightness, trouble breathing, swelling, hives, itching, and rash. Seek emergency help if you experience signs and/or symptoms of an allergic reaction.
- Kidney problems. CYANOKIT can cause kidney problems, including kidney failure. Tell your healthcare provider if you develop crystals in your urine. Your healthcare provider will monitor your kidney function for 7 days after treatment with CYANOKIT, or longer if needed.
- Increased blood pressure. Increased blood pressure is a common but serious side effect during treatment with CYANOKIT. Your healthcare provider will monitor your blood pressure during treatment with CYANOKIT.

The most common side effects of CYANOKIT include:

- red colored urine. Red colored urine redness may last up to 5 weeks after treatment with CYANOKIT.
- acne-like rash. Acne-like rash may appear 7 to 28 daysafter treatment with CYANOKIT. This rash usually goes away without any treatment.

- nausea
- headache
- reactions at the site of infusion

These are not all the side effects with CYANOKIT.
Call your doctor for medical advice about side effects. You may report side effects to FDA at 1-800-FDA-1088.

General information about the safe and effective use of CYANOKIT.
This Patient Information leaflet summarizes the most important information about CYANOKIT. If you would like more information, talk to your healthcare provider. You can ask your pharmacist or healthcare provider for information about CYANOKIT that is written for health professionals.

What are the ingredients in CYANOKIT?
Active ingredient: hydroxocobalamin
Manufactured by: Merck Santé s.a.s., Semoy, France
Distributed by BTG International Inc. West Conshohocken, PA 19428
1-877-377-3784BTG and the BTG roundel logo are registered trademarks of BTG International Ltd.For more information, go to www.CYANOKIT.com.
180_US_20211_NO

This Patient Information has been approved by the U.S. Food and Drug Administration.

Revised: 05/2021

PACKAGE LABEL

Principal Display Panel - 5 g OUTER CARTON

NDC 50633-310-11

CYANOKIT®

(hydroxocobalamin for injection)

5 g per vial

For Intravenous Use

To be reconstituted with 200 mL of 0.9% Sodium Chloride Injection

Diluent Not Included

Kit Contents:

1 Vial, containing Hydroxocobalamin for injection, 5 g

1 Intravenous administration set

1 Transfer spike

1 Quick Use Reference guide

1 Package Insert

BTG

Principal Display Panel - 250 mL Vial Label

CYANOKIT®

(hydroxocobalamin for injection)

5 g per vial

For Intravenous Use

To be reconstituted with 200 mL of 0.9% Sodium Chloride Injection

Diluent Not Included

Rx Only

Manufactured by
Merck Sante s.a.s.

Semoy, France

Distributed by

BTG International Inc.

West Conshohocken, PA 19428

1-877-377-3784

BTG